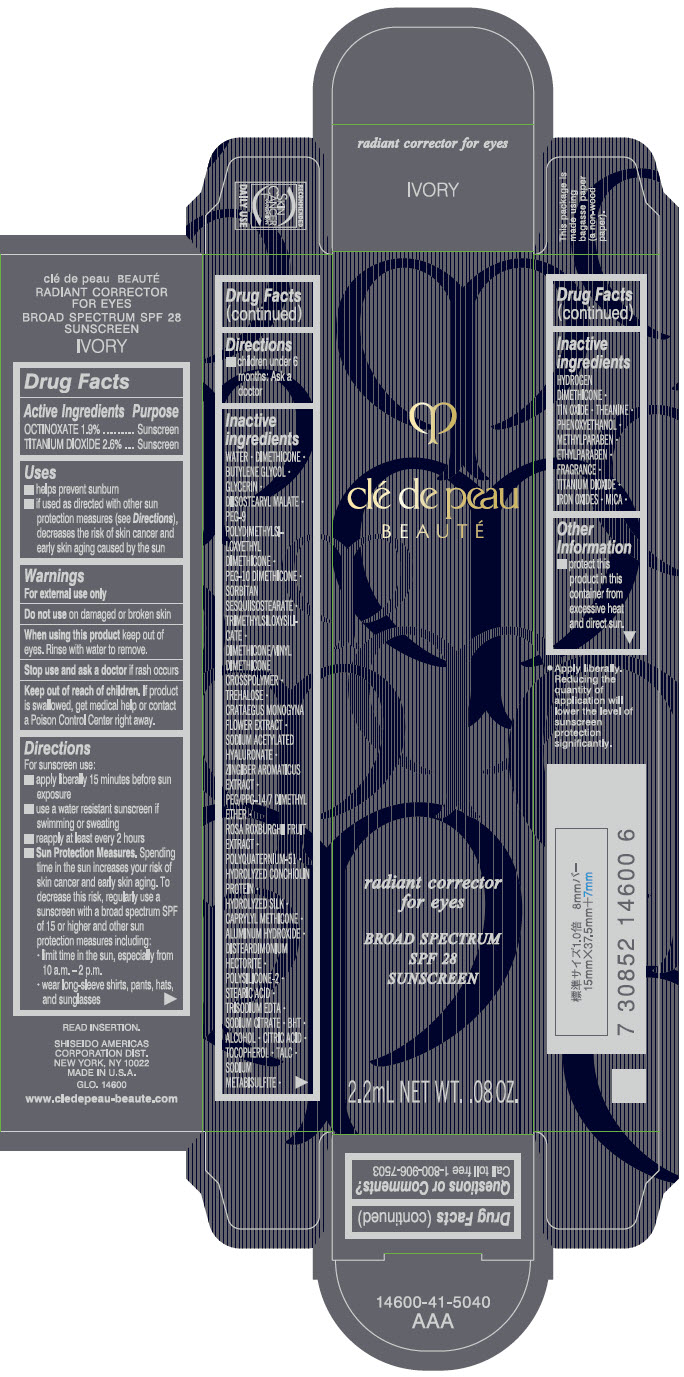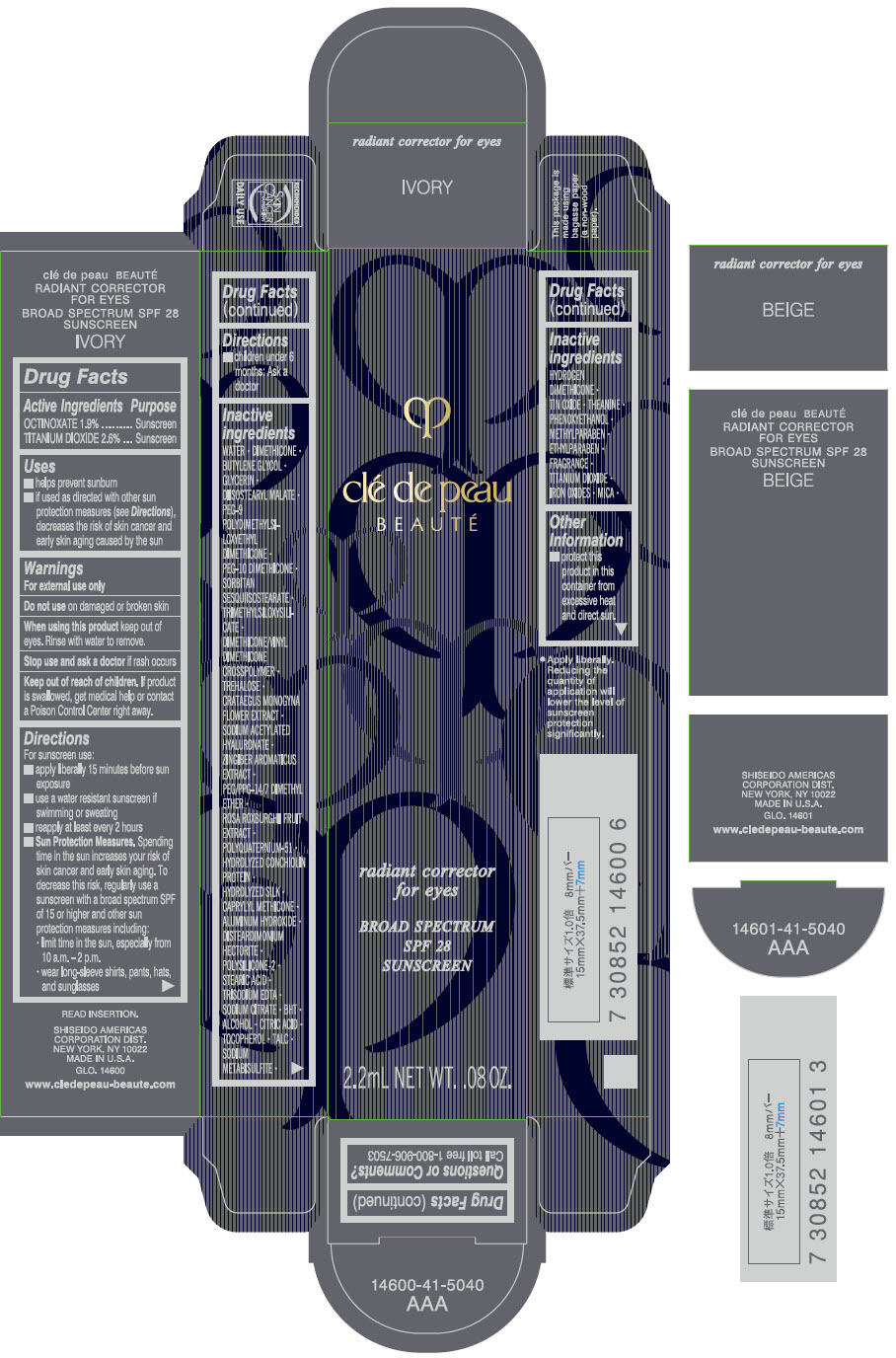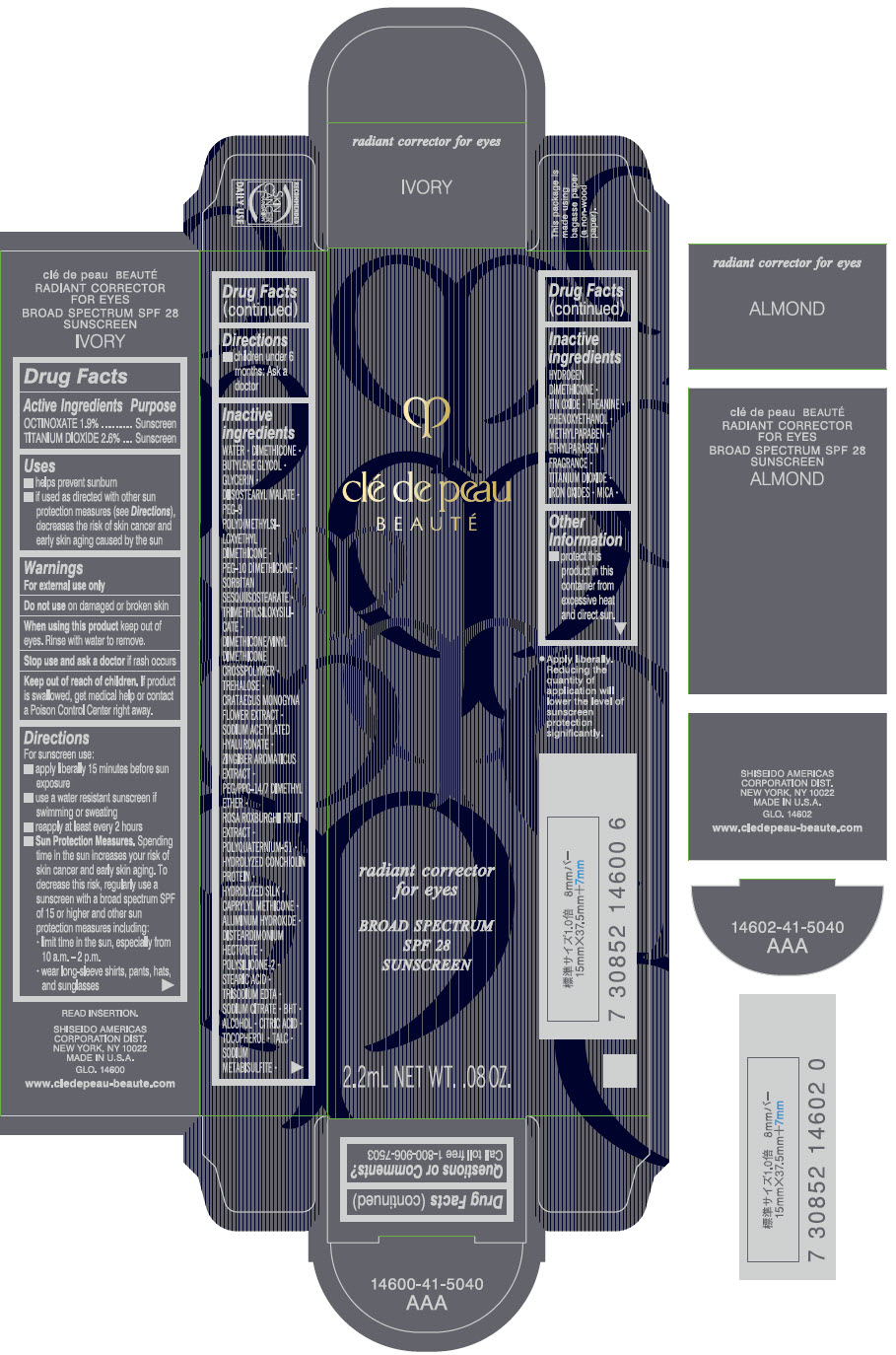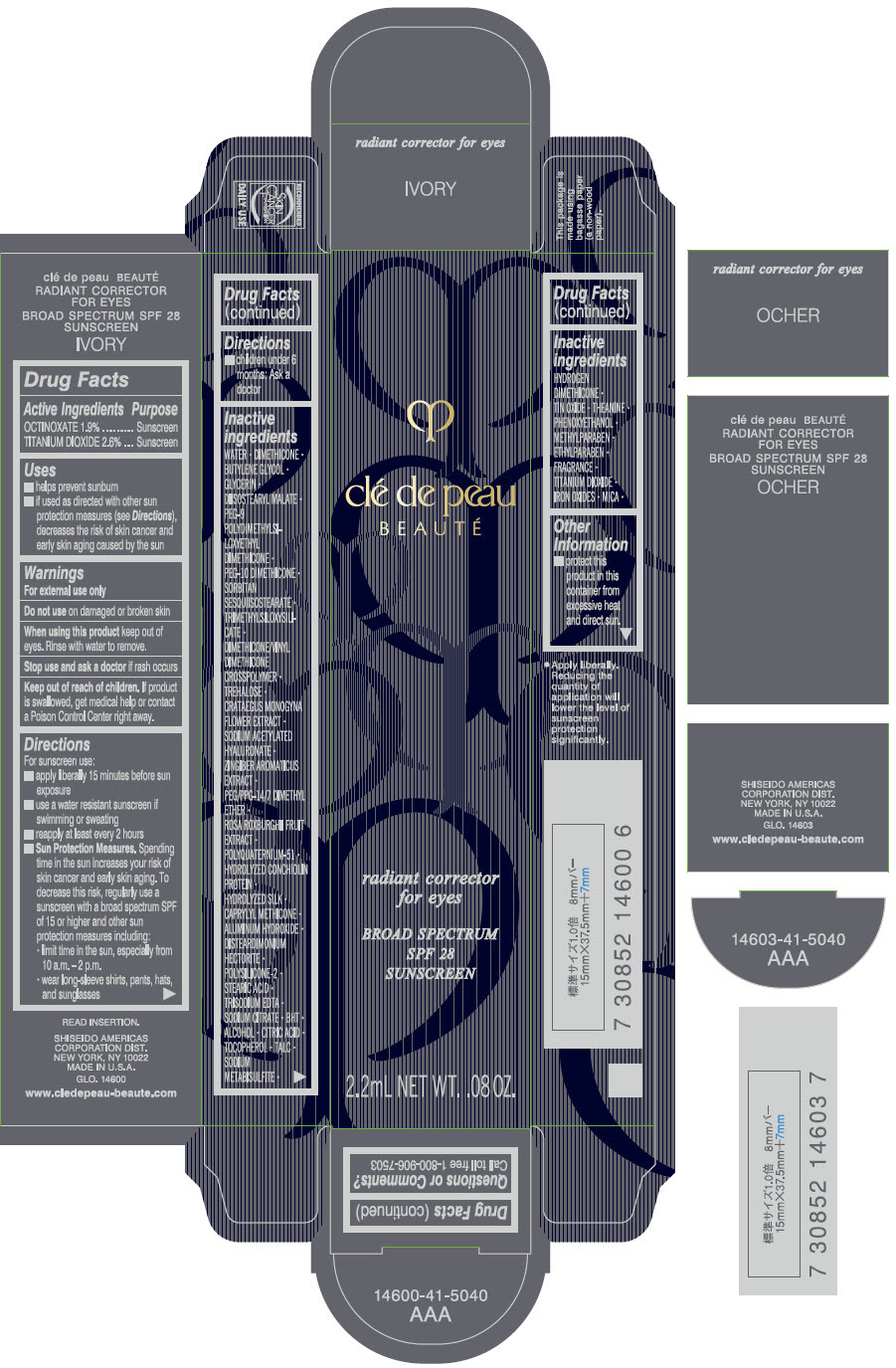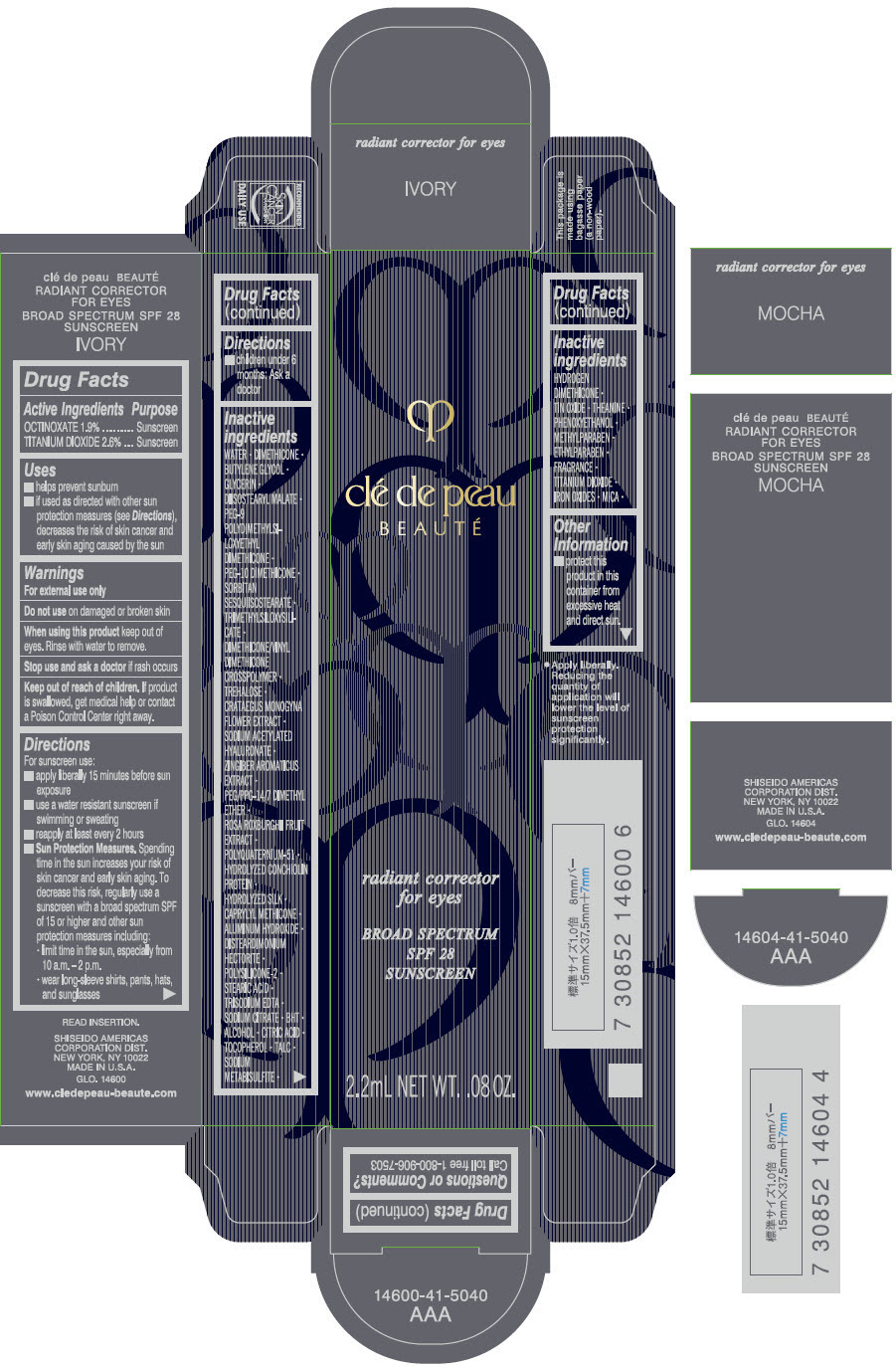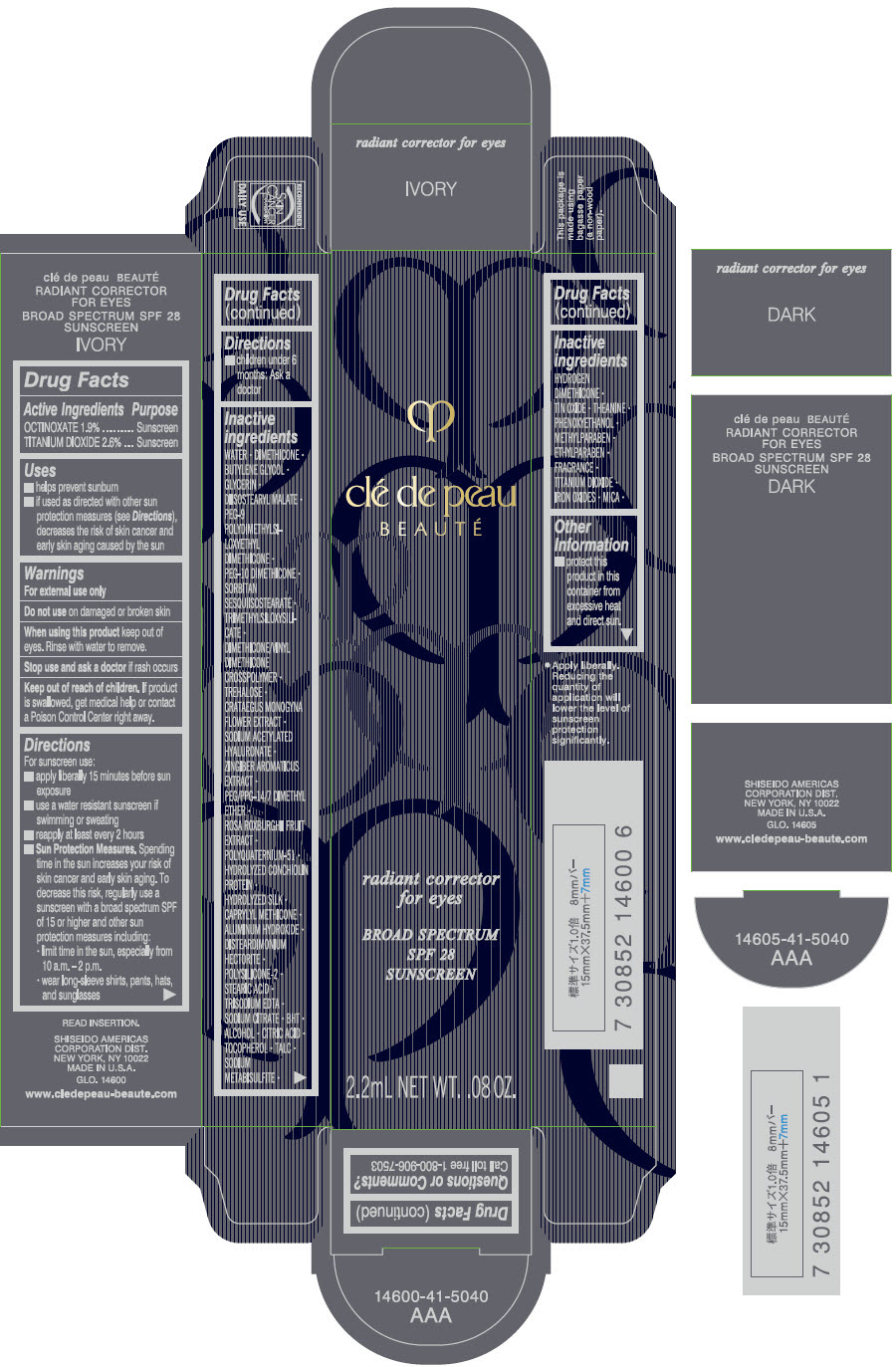 DRUG LABEL: CLE DE PEAU BEAUTE RADIANT CORRECTOR FOR EYES
NDC: 58411-421 | Form: CREAM
Manufacturer: SHISEIDO AMERICAS CORPORATION
Category: otc | Type: HUMAN OTC DRUG LABEL
Date: 20260105

ACTIVE INGREDIENTS: OCTINOXATE 48 mg/2.2 mL; TITANIUM DIOXIDE 65 mg/2.2 mL
INACTIVE INGREDIENTS: WATER; DIMETHICONE; BUTYLENE GLYCOL; GLYCERIN; DIISOSTEARYL MALATE; PEG-9 POLYDIMETHYLSILOXYETHYL DIMETHICONE; PEG-10 DIMETHICONE (600 CST); SORBITAN SESQUIISOSTEARATE; TRIMETHYLSILOXYSILICATE (M/Q 0.6-0.8); DIMETHICONE/VINYL DIMETHICONE CROSSPOLYMER (SOFT PARTICLE); TREHALOSE; CRATAEGUS MONOGYNA FLOWER; SODIUM ACETYLATED HYALURONATE; PEG/PPG-14/7 DIMETHYL ETHER; ROSA ROXBURGHII FRUIT; POLYQUATERNIUM-51 (2-METHACRYLOYLOXYETHYL PHOSPHORYLCHOLINE/N-BUTYL METHACRYLATE; 3:7); CAPRYLYL TRISILOXANE; ALUMINUM HYDROXIDE; DISTEARDIMONIUM HECTORITE; STEARIC ACID; EDETATE TRISODIUM; SODIUM CITRATE, UNSPECIFIED FORM; BUTYLATED HYDROXYTOLUENE; ALCOHOL; CITRIC ACID MONOHYDRATE; .ALPHA.-TOCOPHEROL; TALC; SODIUM METABISULFITE; HYDROGEN DIMETHICONE (13 CST); STANNIC OXIDE; THEANINE; PHENOXYETHANOL; METHYLPARABEN; ETHYLPARABEN; FERRIC OXIDE RED; FERRIC OXIDE YELLOW; FERROSOFERRIC OXIDE; MICA

CLÉ DE PEAU BEAUTÉ RADIANT CORRECTOR FOR EYES

Drug Facts

ACTIVE INGREDIENT

Active ingredients | Purpose
OCTINOXATE 1.9% | Sunscreen
TITANIUM DIOXIDE 2.6% | Sunscreen

Uses

- helps prevent sunburn
- if used as directed with other sun protection measures (see Directions), decreases the risk of skin cancer and early skin aging caused by the sun

Warnings

For external use only

Do not useon damaged or broken skin

WHEN USING

When using this productkeep out of eyes. Rinse with water to remove.

Stop use and ask a doctorif rash occurs

Keep out of reach of children.If product is swallowed, get medical help or contact a Poison Control Center right away.

Directions

For sunscreen use:

- apply liberally 15 minutes before sun exposure
- use a water resistant sunscreen if swimming or sweating
- reapply at least every 2 hours
- Sun Protection Measures. Spending time in the sun increases your risk of skin cancer and early skin aging. To decrease this risk, regularly use a sunscreen with a broad spectrum SPF of 15 or higher and other sun protection measures including:
  - limit time in the sun, especially from 10 a.m. – 2 p.m.
  - wear long-sleeve shirts, pants, hats, and sunglasses
- children under 6 months: Ask a doctor

Inactive Ingredients

WATER•DIMETHICONE•BUTYLENE GLYCOL•GLYCERIN•DIISOSTEARYL MALATE•PEG-9 POLYDIMETHYLSILOXYETHYL DIMETHICONE•PEG-10 DIMETHICONE•SORBITAN SESQUIISOSTEARATE•TRIMETHYLSILOXYSILICATE•DIMETHICONE/VINYL DIMETHICONE CROSSPOLYMER•TREHALOSE•CRATAEGUS MONOGYNA FLOWER EXTRACT•SODIUM ACETYLATED HYALURONATE•ZINGIBER AROMATICUS EXTRACT•PEG/PPG-14/7 DIMETHYL ETHER•ROSA ROXBURGHII FRUIT EXTRACT•POLYQUATERNIUM-51•HYDROLYZED CONCHIOLIN PROTEIN•HYDROLYZED SILK•CAPRYLYL METHICONE•ALUMINUM HYDROXIDE•DISTEARDIMONIUM HECTORITE•POLYSILICONE-2•STEARIC ACID•TRISODIUM EDTA•SODIUM CITRATE•BHT•ALCOHOL•CITRIC ACID•TOCOPHEROL•TALC•SODIUM METABISULFITE•HYDROGEN DIMETHICONE•TIN OXIDE•THEANINE•PHENOXYETHANOL•METHYLPARABEN•ETHYLPARABEN•FRAGRANCE•TITANIUM DIOXIDE•IRON OXIDES•MICA•

Other information

- protect this product in this container from excessive heat and direct sun.

Questions or comments?

Call toll free 1-800-906-7503

PRINCIPAL DISPLAY PANEL - 2.2 mL Tube Carton - IVORY

clé de peau
BEAUTÉ

radiant corrector
for eyes

BROAD SPECTRUM
SPF 28
SUNSCREEN

2.2mL NET WT. .08 OZ.

PRINCIPAL DISPLAY PANEL - 2.2 mL Tube Carton - BEIGE

clé de peau
BEAUTÉ

radiant corrector
for eyes

BROAD SPECTRUM
SPF 28
SUNSCREEN

2.2mL NET WT. .08 OZ.

PRINCIPAL DISPLAY PANEL - 2.2 mL Tube Carton - ALMOND

clé de peau
BEAUTÉ

radiant corrector
for eyes

BROAD SPECTRUM
SPF 28
SUNSCREEN

2.2mL NET WT. .08 OZ.

PRINCIPAL DISPLAY PANEL - 2.2 mL Tube Carton - OCHER

clé de peau
BEAUTÉ

radiant corrector
for eyes

BROAD SPECTRUM
SPF 28
SUNSCREEN

2.2mL NET WT. .08 OZ.

PRINCIPAL DISPLAY PANEL - 2.2 mL Tube Carton - MOCHA

clé de peau
BEAUTÉ

radiant corrector
for eyes

BROAD SPECTRUM
SPF 28
SUNSCREEN

2.2mL NET WT. .08 OZ.

PRINCIPAL DISPLAY PANEL - 2.2 mL Tube Carton - DARK

clé de peau
BEAUTÉ

radiant corrector
for eyes

BROAD SPECTRUM
SPF 28
SUNSCREEN

2.2mL NET WT. .08 OZ.